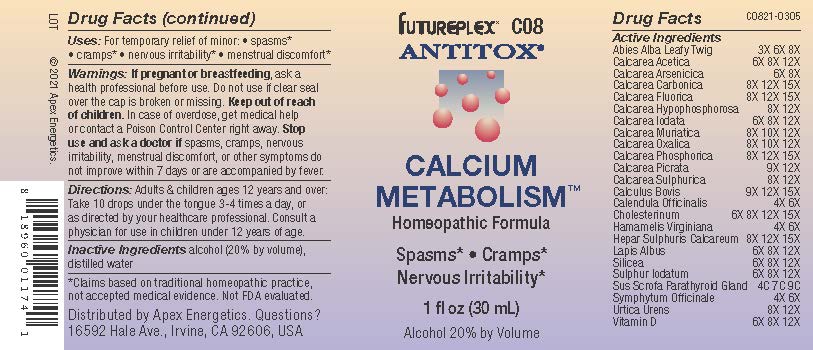 DRUG LABEL: C08
NDC: 63479-0308 | Form: SOLUTION/ DROPS
Manufacturer: Apex Energetics Inc.
Category: homeopathic | Type: HUMAN OTC DRUG LABEL
Date: 20240108

ACTIVE INGREDIENTS: ABIES ALBA LEAFY TWIG 8 [hp_X]/1 mL; CALCIUM ACETATE 12 [hp_X]/1 mL; CALCIUM HYPOPHOSPHITE 12 [hp_X]/1 mL; CALCIUM CHLORIDE 12 [hp_X]/1 mL; CALCIUM OXALATE MONOHYDRATE 12 [hp_X]/1 mL; TRIBASIC CALCIUM PHOSPHATE 15 [hp_X]/1 mL; CALCIUM PICRATE 12 [hp_X]/1 mL; CALENDULA OFFICINALIS FLOWERING TOP 6 [hp_X]/1 mL; CALCIUM HEXAFLUOROSILICATE 12 [hp_X]/1 mL; SULFUR IODIDE 12 [hp_X]/1 mL; BOS TAURUS GALLSTONE 15 [hp_X]/1 mL; URTICA URENS 12 [hp_X]/1 mL; VITAMIN D 12 [hp_X]/1 mL; CHOLESTEROL 15 [hp_X]/1 mL; CALCIUM SULFIDE 15 [hp_X]/1 mL; CALCIUM ARSENATE 8 [hp_X]/1 mL; CALCIUM IODIDE 12 [hp_X]/1 mL; OYSTER SHELL CALCIUM CARBONATE, CRUDE 15 [hp_X]/1 mL; HAMAMELIS VIRGINIANA ROOT BARK/STEM BARK 6 [hp_X]/1 mL; SILICON DIOXIDE 12 [hp_X]/1 mL; CALCIUM FLUORIDE 15 [hp_X]/1 mL; SUS SCROFA PARATHYROID GLAND 9 [hp_C]/1 mL; COMFREY ROOT 6 [hp_X]/1 mL; CALCIUM SULFATE ANHYDROUS 12 [hp_X]/1 mL
INACTIVE INGREDIENTS: ALCOHOL; WATER

C08

Active Ingredients
Abies Alba Leafy Twig | 3X 6X 8X
Calcarea Acetica | 6X 8X 12X
Calcarea Arsenicica | 6X 8X
Calcarea Carbonica | 8X 12X 15X
Calcarea Fluorica | 8X 12X 15X
Calcarea Hypophosphorosa | 8X 12X
Calcarea Iodata | 6X 8X 12X
Calcarea Muriatica | 8X 10X 12X
Calcarea Oxalica | 8X 10X 12X
Calcarea Phosphorica | 8X 12X 15X
Calcarea Picrata | 9X 12X
Calcarea Sulphurica | 8X 12X
Calculus Bovis | 9X 12X 15X
Calendula Officinalis | 4X 6X
Cholesterinum | 6X 8X 12X 15X
Hamamelis Virginiana | 4X 6X
Hepar Sulphuris Calcareum | 8X 12X 15X
Lapis Albus | 6X 8X 12X
Silicea | 6X 8X 12X
Sulphur Iodatum | 6X 8X 12X
Sus Scrofa Parathyroid Gland | 4C 7C 9C
Symphytum Officinale | 4X 6X
Urtica Urens | 8X 12X
Vitamin D | 6X 8X 12X

INDICATIONS AND USAGE

Uses:

For temporary relief of minor:

spasms*

cramps*

nervous irritability*

menstrual discomfort*

*Claims based on traditional homeopathic practice, not accepted medical evidence. Not FDA evaluated.

Warnings:

PREGNANCY OR BREAST FEEDING

If pregnant or breastfeeding, ask a health professional before use.

Do not use if clear seal over the cap is broken or missing.

Keep out of reach of children. In case of overdose, get medical help or contact a Poison Control Center right away.

Stop use and ask a doctor if spasms, cramps, nervous irritability, menstrual discomfort, or other symptoms do not improve within 7 days or are accompanied by fever.

Directions:

Adults & children ages 12 years and over: Take 10 drops under the tongue 3-4 times a day, or as directed by your healthcare professional. Consult a physician for use in children under 12 years of age.

Inactive Ingredients

alcohol (20% by volume), distilled water

Distributed by Apex Energetics. Questions?

16592 Hale Ave., Irvine, CA 92606, USA

PACKAGE LABEL

FUTUREPLEX® C08

ANTITOX®

CALCIUM METABOLISM™

Homeopathic Formula

Spasms*

Cramps*

Nervous Irritability*

1 fl oz (30 mL)

Alcohol 20% by Volume